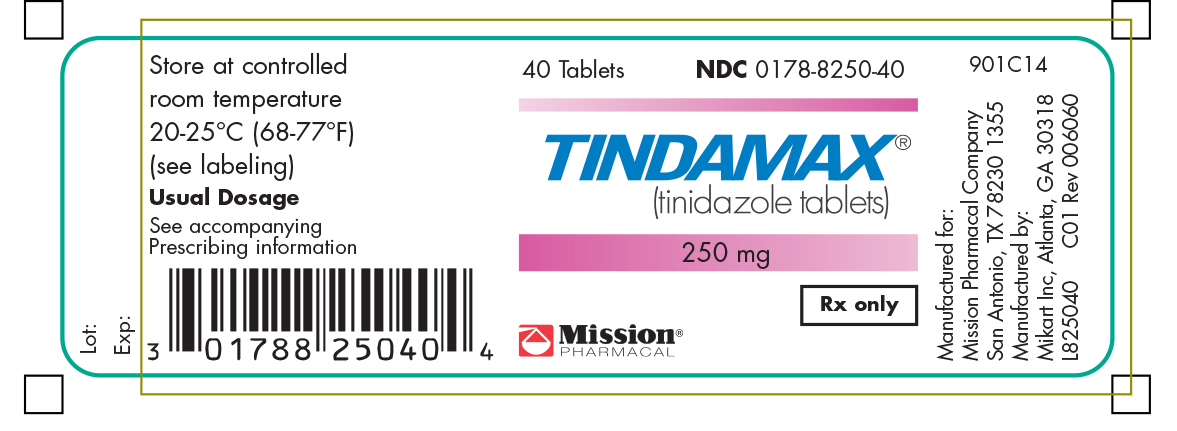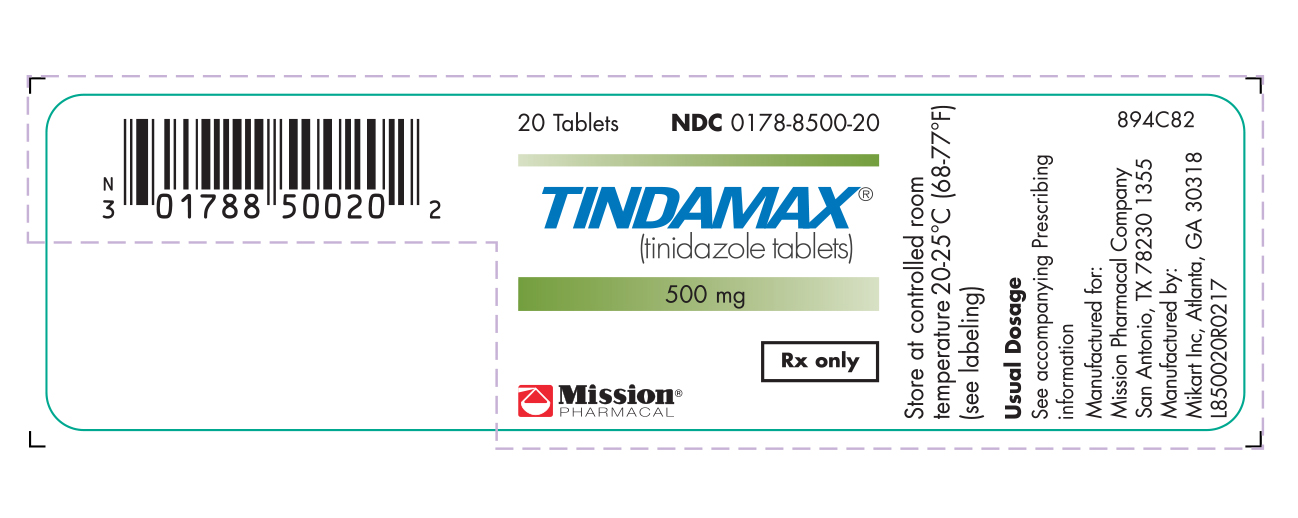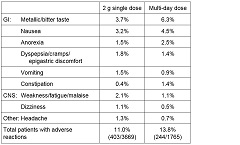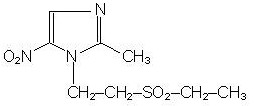 DRUG LABEL: Tindamax
NDC: 0178-8250 | Form: TABLET, FILM COATED
Manufacturer: Mission Pharmacal Company
Category: prescription | Type: HUMAN PRESCRIPTION DRUG LABEL
Date: 20211227

ACTIVE INGREDIENTS: TINIDAZOLE 250 mg/1 1
INACTIVE INGREDIENTS: CROSCARMELLOSE SODIUM; FD&C RED NO. 40; FD&C YELLOW NO. 6; HYPROMELLOSES; MAGNESIUM STEARATE; CELLULOSE, MICROCRYSTALLINE; POLYDEXTROSE; POLYETHYLENE GLYCOL, UNSPECIFIED; STARCH, CORN; TITANIUM DIOXIDE; TRIACETIN; ALUMINUM OXIDE

HIGHLIGHTS OF PRESCRIBING INFORMATION

Tindamax® (tinidazole) oral tablets
These highlights do not include all the information needed to use Tindamax® safely and effectively. See full prescribing information for Tindamax. Tindamax® (tinidazole) oral tablets for oral solution.
Initial U.S. Approval 2004

WARNING: POTENTIAL RISK FOR CARCINOGENICITY

See full prescribing information for complete boxed warning.

Carcinogenicity has been seen in mice and rats treated chronically with metronidazole, another nitroimidazole agent (13.1). Although such data have not been reported for tinidazole, the two drugs are structurally related and have similar biologic effects. Use should be limited to approved indications only.

RECENT MAJOR CHANGES

Contraindications (4) 12/2021

1 INDICATIONS AND USAGE

Tindamax is a nitroimidazole antimicrobial indicated for:

- Trichomoniasis (1.1)
- Giardiasis: in patients age 3 and older (1.2)
- Amebiasis: in patients age 3 and older (1.3)
- Bacterial Vaginosis: in non-pregnant, adult women (1.4, 8.1)

To reduce the development of drug-resistant bacteria and maintain the effectiveness of Tindamax and other antibacterial drugs, Tindamax should be used only to treat or prevent infections that are proven or strongly suspected to be caused by bacteria (1.5).

2 DOSAGE AND ADMINISTRATION

- Trichomoniasis: a single 2 g oral dose taken with food. Treat sexual partners with the same dose and at the same time (2.3)
- Giardiasis: Adults: a single 2 g dose taken with food. Pediatric patients older than three years of age: a single dose of 50 mg/kg (up to 2 g) with food (2.4)
- Amebiasis, Intestinal: Adults: 2 g per day for 3 days with food. Pediatric patients older than three years of age: 50 mg/kg/day (up to 2 g per day) for 3 days with food (2.5). Amebic liver abscess: Adults: 2 g per day for 3-5 days with food. Pediatric patients older than three years of age: 50 mg/kg/day (up to 2 g per day) for 3-5 days with food (2.5)
- Bacterial vaginosis: Non-pregnant, adult women: 2 g once daily for 2 days taken with food, or 1 g once daily for 5 days taken with food (2.6)

3 DOSAGE FORMS AND STRENGTHS

Tablets: 250 mg and 500 mg (3)

4 CONTRAINDICATIONS

- Prior history of hypersensitivity to tinidazole or other nitroimidazole derivatives (4, 6.1, 6.2)
- Patients with Cockayne syndrome (4, 6.2)

5 WARNINGS AND PRECAUTIONS

- Seizures and neuropathy have been reported. Discontinue Tindamax if abnormal neurologic signs develop (5.1)
- Vaginal candidiasis may develop with Tindamax and require treatment with an antifungal agent (5.2)
- Use Tindamax with caution in patients with blood dyscrasias. Tindamax may produce transient leukopenia and neutropenia (5.3, 7.3)

6 ADVERSE REACTIONS

Most common adverse reactions for a single 2 g dose of tinidazole (incidence >1%) are metallic/bitter taste, nausea, weakness/fatigue/malaise, dyspepsia/cramps/epigastric discomfort, vomiting, anorexia, headache, dizziness and constipation (6.1)

To report SUSPECTED ADVERSE REACTIONS, contact Mission Pharmacal Company at 1-800-298-1087 or FDA at 1-800-FDA-1088 or www.fda.gov/medwatch

7 DRUG INTERACTIONS

The following drug interactions were reported for metronidazole, a chemically-related nitroimidazole and may therefore occur with tinidazole:

- Warfarin and other oral coumarin anticoagulants: Anticoagulant dosage may need adjustment during and up to 8 days after tinidazole therapy (7.1)
- Alcohol-containing beverages/preparations: Avoid during and up to 3 days after tinidazole therapy (7.1)
- Lithium: Monitor serum lithium concentrations (7.1)
- Cyclosporine, tacrolimus: Monitor for toxicities of these immunosuppressive drugs (7.1)
- Fluorouracil: Monitor for fluorouracil-associated toxicities (7.1)
- Phenytoin, fosphenytoin: Adjustment of anticonvulsant and/or tinidazole dose(s) may be needed (7.1, 7.2)
- CYP3A4 inducers/inhibitors: Monitor for decreased tinidazole effect or increased adverse reactions (7.2)

8 USE IN SPECIFIC POPULATIONS

- Pediatric Use: Data on tinidazole use in children is limited to treatment of giardiasis and amebiasis in patients age 3 and older (8.4)
- Hemodialysis patients: If tinidazole is administered the same day and prior to hemodialysis, administer an additional ½ dose after end of hemodialysis (8.6, 12.3)

See 17 for PATIENT COUNSELING INFORMATION

Revised: 5/2007

12.4 Microbiology

To reduce the development of drug-resistant bacteria and maintain the effectiveness of Tindamax and other antibacterial drugs, Tindamax should be used only to treat or prevent infections that are proven or strongly suspected to be caused by bacteria.

FULL PRESCRIBING INFORMATION

WARNING: POTENTIAL RISK FOR CARCINOGENICITY

Carcinogenicity has been seen in mice and rats treated chronically with metronidazole, another nitroimidazole agent (13.1). Although such data have not been reported for tinidazole, the two drugs are structurally related and have similar biologic effects. Its use should be reserved for the conditions described in INDICATIONS AND USAGE (1).

1 INDICATIONS AND USAGE

1.1 Trichomoniasis

Tinidazole is indicated for the treatment of trichomoniasis caused by Trichomonas vaginalis. The organism should be identified by appropriate diagnostic procedures. Because trichomoniasis is a sexually transmitted disease with potentially serious sequelae, partners of infected patients should be treated simultaneously in order to prevent re-infection [see Clinical Studies (14.1)].

1.2 Giardiasis

Tinidazole is indicated for the treatment of giardiasis caused by Giardia duodenalis (also termed G. lamblia) in both adults and pediatric patients older than three years of age [see Clinical Studies (14.2)].

1.3 Amebiasis

Tinidazole is indicated for the treatment of intestinal amebiasis and amebic liver abscess caused by Entamoeba histolytica in both adults and pediatric patients older than three years of age. It is not indicated in the treatment of asymptomatic cyst passage [see Clinical Studies (14.3, 14.4)].

1.4 Bacterial Vaginosis

Tinidazole is indicated for the treatment of bacterial vaginosis (formerly referred to as Haemophilus vaginitis, Gardnerella vaginitis, nonspecific vaginitis, or anaerobic vaginosis) in adult women [see Use in Specific Populations (8.1) and Clinical Studies (14.5)].

Other pathogens commonly associated with vulvovaginitis such as Trichomonas vaginalis, Chlamydia trachomatis, Neisseria gonorrhoeae, Candida albicans and Herpes simplex virus should be ruled out.

1.5 Usage

To reduce the development of drug-resistant bacteria and maintain the effectiveness of Tindamax and other antibacterial drugs, Tindamax should be used only to treat or prevent infections that are proven or strongly suspected to be caused by susceptible bacteria. When culture and susceptibility information are available, they should be considered in selecting or modifying antibacterial therapy. In the absence of such data, local epidemiology and susceptibility patterns may contribute to the empiric selection of therapy.

2 DOSAGE AND ADMINISTRATION

2.1 Dosing Instructions

It is advisable to take tinidazole with food to minimize the incidence of epigastric discomfort and other gastrointestinal side-effects. Food does not affect the oral bioavailability of tinidazole [see Clinical Pharmacology (12.3)].

Alcoholic beverages should be avoided when taking tinidazole and for 3 days afterwards [see Drug Interactions (7.1)].

2.2 Compounding of the Oral Suspension

For those unable to swallow tablets, tinidazole tablets may be crushed in artificial cherry syrup to be taken with food.

Procedure for Extemporaneous Pharmacy Compounding of the Oral Suspension: Pulverize four 500 mg oral tablets with a mortar and pestle. Add approximately 10 mL of cherry syrup to the powder and mix until smooth. Transfer the suspension to a graduated amber container. Use several small rinses of cherry syrup to transfer any remaining drug in the mortar to the final suspension for a final volume of 30 mL. The suspension of crushed tablets in artificial cherry syrup is stable for 7 days at room temperature. When this suspension is used, it should be shaken well before each administration.

2.3 Trichomoniasis

The recommended dose in both females and males is a single 2 g oral dose taken with food. Since trichomoniasis is a sexually transmitted disease, sexual partners should be treated with the same dose and at the same time.

2.4 Giardiasis

The recommended dose in adults is a single 2 g dose taken with food. In pediatric patients older than three years of age, the recommended dose is a single dose of 50 mg/kg (up to 2 g) with food.

2.5 Amebiasis

Intestinal: The recommended dose in adults is a 2 g dose per day for 3 days taken with food. In pediatric patients older than three years of age, the recommended dose is 50 mg/kg/day (up to 2 g per day) for 3 days with food.

Amebic Liver Abscess: The recommended dose in adults is a 2 g dose per day for 3-5 days taken with food. In pediatric patients older than three years of age, the recommended dose is 50 mg/kg/day (up to 2 g per day) for 3-5 days with food. There are limited pediatric data on durations of therapy exceeding 3 days, although a small number of children were treated for 5 days without additional reported adverse reactions. Children should be closely monitored when treatment durations exceed 3 days.

2.6 Bacterial Vaginosis

The recommended dose in non-pregnant females is a 2 g oral dose once daily for 2 days taken with food or a 1 g oral dose once daily for 5 days taken with food. The use of tinidazole in pregnant patients has not been studied for bacterial vaginosis.

3 DOSAGE FORMS AND STRENGTHS

- 250 mg tablets are pink, round, scored tablets, with TM debossed on one side and 250 on the other
- 500 mg tablets are pink, oval, scored tablets, with TM debossed on one side and 500 on the other

4 CONTRAINDICATIONS

The use of tinidazole is contraindicated:

- In patients with a previous history of hypersensitivity to tinidazole or other nitroimidazole derivatives. Reported reactions have ranged in severity from urticaria to Stevens-Johnson syndrome [see Adverse Reactions (6.1, 6.2)].
- In patients with Cockayne syndrome. Severe irreversible hepatotoxicity/acute liver failure with fatal outcomes have been reported after initiation of metronidazole, another nitroimidazole drug, structurally related to tinidazole, in patients with Cockayne syndrome [see Adverse Reactions (6.2)]

5 WARNINGS AND PRECAUTIONS

5.1 Neurological Adverse Reactions

Convulsive seizures and peripheral neuropathy, the latter characterized mainly by numbness or paresthesia of an extremity, have been reported in patients treated with tinidazole. The appearance of abnormal neurologic signs demands the prompt discontinuation of tinidazole therapy.

5.2 Vaginal Candidiasis

The use of tinidazole may result in Candida vaginitis. In a clinical study of 235 women who received tinidazole for bacterial vaginosis, a vaginal fungal infection developed in 11 (4.7%) of all study subjects [see Clinical Studies (14.5)].

5.3 Blood Dyscrasia

Tinidazole should be used with caution in patients with evidence of or history of blood dyscrasia [see Drug Interactions (7.3)].

5.4 Drug Resistance

Prescribing Tindamax in the absence of a proven or strongly suspected bacterial infection or a prophylactic indication is unlikely to provide benefit to the patient and increases the risk of the development of drug-resistant bacteria.

6 ADVERSE REACTIONS

6.1 Clinical Studies Experience

Because clinical trials are conducted under widely varying conditions, adverse reaction rates observed in the clinical trials of a drug cannot be directly compared to rates in the clinical trials of another drug and may not reflect the rates observed in practice.

Among 3669 patients treated with a single 2 g dose of tinidazole, in both controlled and uncontrolled trichomoniasis and giardiasis clinical studies, adverse reactions were reported by 11.0% of patients. For multi-day dosing in controlled and uncontrolled amebiasis studies, adverse reactions were reported by 13.8% of 1765 patients. Common (≥ 1% incidence) adverse reactions reported by body system are as follows. (Note: Data described in Table 1 below are pooled from studies with variable designs and safety evaluations.)

Other adverse reactions reported with tinidazole include:

Central Nervous System: Two serious adverse reactions reported include convulsions and transient peripheral neuropathy including numbness and paresthesia [see Warnings and Precautions (5.1)]. Other CNS reports include vertigo, ataxia, giddiness, insomnia, drowsiness.

Gastrointestinal: tongue discoloration, stomatitis, diarrhea

Hypersensitivity: urticaria, pruritis, rash, flushing, sweating, dryness of mouth, fever, burning sensation, thirst, salivation, angioedema

Renal: darkened urine

Cardiovascular: palpitations

Hematopoietic: transient neutropenia, transient leukopenia

Other: Candida overgrowth, increased vaginal discharge, oral candidiasis, hepatic abnormalities including raised transaminase level, arthralgias, myalgias, and arthritis.

Table 1. Adverse Reactions Summary of Published Reports

Adverse Reactions in Pediatric Patients: In pooled pediatric studies, adverse reactions reported in pediatric patients taking tinidazole were similar in nature and frequency to adult findings including nausea, vomiting, diarrhea, taste change, anorexia, and abdominal pain. Rare reported adverse reactions include bronchospasm, dyspnea, coma, confusion, depression, furry tongue, pharyngitis and reversible thrombocytopenia.

Bacterial vaginosis: The most common adverse reactions in treated patients (incidence >2%), which were not identified in the trichomoniasis, giardiasis and amebiasis studies, are gastrointestinal: decreased appetite, and flatulence; renal: urinary tract infection, painful urination, and urine abnormality; and other reactions including pelvic pain, vulvo-vaginal discomfort, vaginal odor, menorrhagia, and upper respiratory tract infection [See Clinical Studies (14.5)].

6.2 Postmarketing Experience

The following adverse reactions have been identified and reported during post-approval use of Tindamax or other nitroimidazole agents. Because the reports of these reactions are voluntary and the population is of uncertain size, it is not always possible to reliably estimate the frequency of the reaction or establish a causal relationship to drug exposure.

Tindamax:

Severe acute hypersensitivity reactions have been reported on initial or subsequent exposure to tinidazole. Hypersensitivity reactions may include urticaria, pruritis, angioedema, Stevens-Johnson syndrome and erythema multiforme.

Metronidazole, Another Nitroimidazole Product, Structurally Related to Tinidazole:

Cases of severe irreversible hepatotoxicity/acute liver failure, including cases with fatal outcomes with very rapid onset after initiation of systemic use of metronidazole, another nitroimidazole agent structurally related to tinidazole, have been reported in patients with Cockayne syndrome (latency from drug start to signs of liver failure as short as 2 days) [see Contraindications (4)].

6.1 Clinical Studies Experience

Because clinical trials are conducted under widely varying conditions, adverse reaction rates observed in the clinical trials of a drug cannot be directly compared to rates in the clinical trials of another drug and may not reflect the rates observed in practice.

Among 3669 patients treated with a single 2 g dose of tinidazole, in both controlled and uncontrolled trichomoniasis and giardiasis clinical studies, adverse reactions were reported by 11.0% of patients. For multi-day dosing in controlled and uncontrolled amebiasis studies, adverse reactions were reported by 13.8% of 1765 patients. Common (≥ 1% incidence) adverse reactions reported by body system are as follows. (Note: Data described in Table 1 below are pooled from studies with variable designs and safety evaluations.)

Other adverse reactions reported with tinidazole include:

Central Nervous System: Two serious adverse reactions reported include convulsions and transient peripheral neuropathy including numbness and paresthesia [see Warnings and Precautions (5.1)]. Other CNS reports include vertigo, ataxia, giddiness, insomnia, drowsiness.

Gastrointestinal: tongue discoloration, stomatitis, diarrhea

Hypersensitivity: urticaria, pruritis, rash, flushing, sweating, dryness of mouth, fever, burning sensation, thirst, salivation, angioedema

Renal: darkened urine

Cardiovascular: palpitations

Hematopoietic: transient neutropenia, transient leukopenia

Other: Candida overgrowth, increased vaginal discharge, oral candidiasis, hepatic abnormalities including raised transaminase level, arthralgias, myalgias, and arthritis.

Table 1. Adverse Reactions Summary of Published Reports
 | 2 g single dose | Multi-day dose
GI: Metallic/bitter taste | 3.7% | 6.3%
Nausea | 3.2% | 4.5%
Anorexia | 1.5% | 2.5%
Dyspepsia/cramps/epigastric discomfort | 1.8% | 1.4%
Vomiting | 1.5% | 0.9%
Constipation | 0.4% | 1.4%
CNS: Weakness/fatigue/malaise | 2.1% | 1.1%
Dizziness | 1.1% | 0.5%
Other: Headache | 1.3% | 0.7%
Total patients with adverse reactions | 11.0% (403/3669) | 13.8% (244/1765)

Rare reported adverse reactions include bronchospasm, dyspnea, coma, confusion, depression, furry tongue, pharyngitis and reversible thrombocytopenia.

Adverse Reactions in Pediatric Patients: In pooled pediatric studies, adverse reactions reported in pediatric patients taking tinidazole were similar in nature and frequency to adult findings including nausea, vomiting, diarrhea, taste change, anorexia, and abdominal pain.

Bacterial vaginosis: The most common adverse reactions in treated patients (incidence >2%), which were not identified in the trichomoniasis, giardiasis and amebiasis studies, are gastrointestinal: decreased appetite, and flatulence; renal: urinary tract infection, painful urination, and urine abnormality; and other reactions including pelvic pain, vulvo-vaginal discomfort, vaginal odor, menorrhagia, and upper respiratory tract infection [See Clinical Studies (14.5)].

6.2 Postmarketing Experience

The following adverse reactions have been identified and reported during post-approval use of Tindamax. Because the reports of these reactions are voluntary and the population is of uncertain size, it is not always possible to reliably estimate the frequency of the reaction or establish a causal relationship to drug exposure.

Severe acute hypersensitivity reactions have been reported on initial or subsequent exposure to tinidazole. Hypersensitivity reactions may include urticaria, pruritis, angioedema, Stevens-Johnson syndrome and erythema multiforme.

7 DRUG INTERACTIONS

Although not specifically identified in studies with tinidazole, the following drug interactions were reported for metronidazole, a chemically-related nitroimidazole. Therefore, these drug interactions may occur with tinidazole.

7.1 Potential Effects of Tinidazole on Other Drugs

Warfarin and Other Oral Coumarin Anticoagulants: As with metronidazole, tinidazole may enhance the effect of warfarin and other coumarin anticoagulants, resulting in a prolongation of prothrombin time. The dosage of oral anticoagulants may need to be adjusted during tinidazole co-administration and up to 8 days after discontinuation.

Alcohols, Disulfiram: Alcoholic beverages and preparations containing ethanol or propylene glycol should be avoided during tinidazole therapy and for 3 days afterward because abdominal cramps, nausea, vomiting, headaches, and flushing may occur. Psychotic reactions have been reported in alcoholic patients using metronidazole and disulfiram concurrently. Though no similar reactions have been reported with tinidazole, tinidazole should not be given to patients who have taken disulfiram within the last two weeks.

Lithium: Metronidazole has been reported to elevate serum lithium levels. It is not known if tinidazole shares this property with metronidazole, but consideration should be given to measuring serum lithium and creatinine levels after several days of simultaneous lithium and tinidazole treatment to detect potential lithium intoxication.

Phenytoin, Fosphenytoin: Concomitant administration of oral metronidazole and intravenous phenytoin was reported to result in prolongation of the half-life and reduction in the clearance of phenytoin. Metronidazole did not significantly affect the pharmacokinetics of orally-administered phenytoin.

Cyclosporine, Tacrolimus: There are several case reports suggesting that metronidazole has the potential to increase the levels of cyclosporine and tacrolimus. During tinidazole co-administration with either of these drugs, the patient should be monitored for signs of calcineurin-inhibitor associated toxicities.

Fluorouracil: Metronidazole was shown to decrease the clearance of fluorouracil, resulting in an increase in side-effects without an increase in therapeutic benefits. If the concomitant use of tinidazole and fluorouracil cannot be avoided, the patient should be monitored for fluorouracil-associated toxicities.

7.2 Potential Effects of Other Drugs on Tinidazole

CYP3A4 Inducers and Inhibitors: Simultaneous administration of tinidazole with drugs that induce liver microsomal enzymes, i.e., CYP3A4 inducers such as phenobarbital, rifampin, phenytoin, and fosphenytoin (a pro-drug of phenytoin), may accelerate the elimination of tinidazole, decreasing the plasma level of tinidazole. Simultaneous administration of drugs that inhibit the activity of liver microsomal enzymes, i.e., CYP3A4 inhibitors such as cimetidine and ketoconazole, may prolong the half-life and decrease the plasma clearance of tinidazole, increasing the plasma concentrations of tinidazole.

Cholestyramine: Cholestyramine was shown to decrease the oral bioavailability of metronidazole by 21%. Thus, it is advisable to separate dosing of cholestyramine and tinidazole to minimize any potential effect on the oral bioavailability of tinidazole.

Oxytetracycline: Oxytetracycline was reported to antagonize the therapeutic effect of metronidazole.

7.3 Laboratory Test Interactions

Tinidazole, like metronidazole, may interfere with certain types of determinations of serum chemistry values, such as aspartate aminotransferase (AST, SGOT), alanine aminotransferase (ALT, SGPT), lactate dehydrogenase (LDH), triglycerides, and hexokinase glucose. Values of zero may be observed. All of the assays in which interference has been reported involve enzymatic coupling of the assay to oxidation-reduction of nicotinamide adenine dinucleotide (NAD^+↔ NADH). Potential interference is due to the similarity of absorbance peaks of NADH and tinidazole.

Tinidazole, like metronidazole, may produce transient leukopenia and neutropenia; however, no persistent hematological abnormalities attributable to tinidazole have been observed in clinical studies. Total and differential leukocyte counts are recommended if re-treatment is necessary.

8 USE IN SPECIFIC POPULATIONS

8.1 Pregnancy

Teratogenic effects: Pregnancy Category C

The use of tinidazole in pregnant patients has not been studied. Since tinidazole crosses the placental barrier and enters fetal circulation it should not be administered to pregnant patients in the first trimester.

Embryo-fetal developmental toxicity studies in pregnant mice indicated no embryo-fetal toxicity or malformations at the highest dose level of 2,500 mg/kg (approximately 6.3-fold the highest human therapeutic dose based upon body surface area conversions). In a study with pregnant rats a slightly higher incidence of fetal mortality was observed at a maternal dose of 500 mg/kg (2.5-fold the highest human therapeutic dose based upon body surface area conversions). No biologically relevant neonatal developmental effects were observed in rat neonates following maternal doses as high as 600 mg/kg (3-fold the highest human therapeutic dose based upon body surface area conversions). Although there is some evidence of mutagenic potential and animal reproduction studies are not always predictive of human response, the use of tinidazole after the first trimester of pregnancy requires that the potential benefits of the drug be weighed against the possible risks to both the mother and the fetus.

8.3 Nursing Mothers

Tinidazole is excreted in breast milk in concentrations similar to those seen in serum. Tinidazole can be detected in breast milk for up to 72 hours following administration. Interruption of breast-feeding is recommended during tinidazole therapy and for 3 days following the last dose.

8.4 Pediatric Use

Other than for use in the treatment of giardiasis and amebiasis in pediatric patients older than three years of age, safety and effectiveness of tinidazole in pediatric patients have not been established.

Pediatric Administration: For those unable to swallow tablets, tinidazole tablets may be crushed in artificial cherry syrup, to be taken with food [see Dosage and Administration (2.2)].

8.5 Geriatric Use

Clinical studies of tinidazole did not include sufficient numbers of subjects aged 65 and over to determine whether they respond differently from younger subjects. In general, dose selection for an elderly patient should be cautious, reflecting the greater frequency of decreased hepatic, renal, or cardiac function, and of concomitant disease or other drug therapy.

8.6 Renal Impairment

Because the pharmacokinetics of tinidazole in patients with severe renal impairment (CrCL < 22 mL/min) are not significantly different from those in healthy subjects, no dose adjustments are necessary in these patients.

Patients undergoing hemodialysis: If tinidazole is administered on the same day as and prior to hemodialysis, it is recommended that an additional dose of tinidazole equivalent to one-half of the recommended dose be administered after the end of the hemodialysis [see Clinical Pharmacology (12.3)].

8.7 Hepatic Impairment

There are no data on tinidazole pharmacokinetics in patients with impaired hepatic function. Reduced elimination of metronidazole, a chemically-related nitroimidazole, has been reported in this population. Usual recommended doses of tinidazole should be administered cautiously in patients with hepatic dysfunction [see Clinical Pharmacology (12.3)].

10 OVERDOSAGE

There are no reported overdoses with tinidazole in humans.

Treatment of Overdosage: There is no specific antidote for the treatment of overdosage with tinidazole; therefore, treatment should be symptomatic and supportive. Gastric lavage may be helpful. Hemodialysis can be considered because approximately 43% of the amount present in the body is eliminated during a 6-hour hemodialysis session.

11 DESCRIPTION

Tinidazole is a synthetic antiprotozoal and antibacterial agent. It is 1-[2-(ethylsulfonyl)ethyl]-2-methyl-5-nitroimidazole, a second-generation 2-methyl-5-nitroimidazole, which has the following chemical structure:

Tindamax pink oral tablets contain 250 mg or 500 mg of tinidazole. Inactive ingredients include croscarmellose sodium, FD&C Red 40 lake, FD&C Yellow 6 lake, hypromellose, magnesium stearate, microcrystalline cellulose, polydextrose, polyethylene glycol, pregelatinized corn starch, titanium dioxide, and triacetin.

12 CLINICAL PHARMACOLOGY

12.1 Mechanism of Action

Tinidazole is an antiprotozoal, antibacterial agent. [See Clinical Pharmacology (12.4)].

12.3 Pharmacokinetics

Absorption: After oral administration, tinidazole is rapidly and completely absorbed. A bioavailability study of Tindamax tablets was conducted in adult healthy volunteers. All subjects received a single oral dose of 2 g (four 500 mg tablets) of Tindamax following an overnight fast. Oral administration of four 500 mg tablets of Tindamax under fasted conditions produced a mean peak plasma concentration (Cmax) of 47.7 (±7.5) µg/mL with a mean time to peak concentration (Tmax) of 1.6 (±0.7) hours, and a mean area under the plasma concentration-time curve (AUC, 0-∞) of 901.6 (± 126.5) µg/hr/mL at 72 hours. The elimination half-life (T1/2) was 13.2 (±1.4) hours. Mean plasma levels decreased to 14.3 µg/mL at 24 hours, 3.8 µg/mL at 48 hours and 0.8 µg/mL at 72 hours following administration. Steady-state conditions are reached in 2½ - 3 days of multi-day dosing.

Administration of Tindamax tablets with food resulted in a delay in Tmax of approximately 2 hours and a decline in Cmax of approximately 10%, compared to fasted conditions. However, administration of Tindamax with food did not affect AUC or T1/2 in this study.

In healthy volunteers, administration of crushed Tindamax tablets in artificial cherry syrup, [prepared as described in Dosage and Administration (2.2) ] after an overnight fast had no effect on any pharmacokinetic parameter as compared to tablets swallowed whole under fasted conditions.

Distribution: Tinidazole is distributed into virtually all tissues and body fluids and also crosses the blood-brain barrier. The apparent volume of distribution is about 50 liters. Plasma protein binding of tinidazole is 12%. Tinidazole crosses the placental barrier and is secreted in breast milk.

Metabolism: Tinidazole is significantly metabolized in humans prior to excretion. Tinidazole is partly metabolized by oxidation, hydroxylation, and conjugation. Tinidazole is the major drug-related constituent in plasma after human treatment, along with a small amount of the 2-hydroxymethyl metabolite.

Tinidazole is biotransformed mainly by CYP3A4. In an in vitro metabolic drug interaction study, tinidazole concentrations of up to 75 µg/mL did not inhibit the enzyme activities of CYP1A2, CYP2B6, CYP2C9, CYP2D6, CYP2E1, and CYP3A4.

The potential of tinidazole to induce the metabolism of other drugs has not been evaluated.

Elimination: The plasma half-life of tinidazole is approximately 12-14 hours. Tinidazole is excreted by the liver and the kidneys. Tinidazole is excreted in the urine mainly as unchanged drug (approximately 20-25% of the administered dose). Approximately 12% of the drug is excreted in the feces.

Patients with impaired renal function: The pharmacokinetics of tinidazole in patients with severe renal impairment (CrCL < 22 mL/min) are not significantly different from the pharmacokinetics seen in healthy subjects. However, during hemodialysis, clearance of tinidazole is significantly increased; the half-life is reduced from 12.0 hours to 4.9 hours. Approximately 43% of the amount present in the body is eliminated during a 6-hour hemodialysis session [see Use in Specific Populations (8.6)]. The pharmacokinetics of tinidazole in patients undergoing routine continuous peritoneal dialysis have not been investigated.

Patients with impaired hepatic function: There are no data on tinidazole pharmacokinetics in patients with impaired hepatic function. Reduction of metabolic elimination of metronidazole, a chemically-related nitroimidazole, in patients with hepatic dysfunction has been reported in several studies [see Use in Specific Populations (8.7)].

12.4 Microbiology

Mechanism of Action: Tinidazole is an antiprotozoal, antibacterial agent. The nitro- group of tinidazole is reduced by cell extracts of Trichomonas. The free nitro- radical generated as a result of this reduction may be responsible for the antiprotozoal activity. Chemically reduced tinidazole was shown to release nitrites and cause damage to purified bacterial DNA in vitro. Additionally, the drug caused DNA base changes in bacterial cells and DNA strand breakage in mammalian cells. The mechanism by which tinidazole exhibits activity against Giardia and Entamoeba species is not known.

Antibacterial: Culture and sensitivity testing of bacteria are not routinely performed to establish the diagnosis of bacterial vaginosis [see Indications and Usage (1.4)]; standard methodology for the susceptibility testing of potential bacterial pathogens, Gardnerella vaginalis, Mobiluncus spp. or Mycoplasma hominis, has not been defined. The following in vitro data are available, but their clinical significance is unknown. Tinidazole is active in vitro against most strains of the following organisms that have been reported to be associated with bacterial vaginosis:

- Bacteroides spp.
- Gardnerella vaginalis
- Prevotella spp.

Tinidazole does not appear to have activity against most strains of vaginal lactobacilli.

Antiprotozoal: Tinidazole demonstrates activity both in vitro and in clinical infections against the following protozoa: Trichomonas vaginalis; Giardia duodenalis (also termed G. lamblia); and Entamoeba histolytica.

For protozoal parasites, standardized susceptibility tests do not exist for use in clinical microbiology laboratories.

Drug Resistance: The development of resistance to tinidazole by G. duodenalis, E. histolytica, or bacteria associated with bacterial vaginosis has not been examined.

Cross-resistance: Approximately 38% of T. vaginalis isolates exhibiting reduced susceptibility to metronidazole also show reduced susceptibility to tinidazole in vitro. The clinical significance of such an effect is not known.

13 NONCLINICAL TOXICOLOGY

13.1 Carcinogenesis, Mutagenesis, Impairment of Fertility

Metronidazole, a chemically-related nitroimidazole, has been reported to be carcinogenic in mice and rats but not hamsters. In several studies metronidazole showed evidence of pulmonary, hepatic, and lymphatic tumorigenesis in mice and mammary and hepatic tumors in female rats. Tinidazole carcinogenicity studies in rats, mice or hamsters have not been reported.

Tinidazole was mutagenic in the TA 100, S. typhimurium tester strain both with and without the metabolic activation system and was negative for mutagenicity in the TA 98 strain. Mutagenicity results were mixed (positive and negative) in the TA 1535, 1537, and 1538 strains. Tinidazole was also mutagenic in a tester strain of Klebsiella pneumonia. Tinidazole was negative for mutagenicity in a mammalian cell culture system utilizing Chinese hamster lung V79 cells (HGPRT test system) and negative for genotoxicity in the Chinese hamster ovary (CHO) sister chromatid exchange assay. Tinidazole was positive for in vivo genotoxicity in the mouse micronucleus assay.

In a 60-day fertility study, tinidazole reduced fertility and produced testicular histopathology in male rats at a 600 mg/kg/day dose level (approximately 3-fold the highest human therapeutic dose based upon body surface area conversions). Spermatogenic effects resulted from 300 and 600 mg/kg/day dose levels. The no observed adverse reaction level for testicular and spermatogenic effects was 100 mg/kg/day (approximately 0.5-fold the highest human therapeutic dose based upon body surface area conversions). This effect is characteristic of agents in the 5-nitroimidazole class.

13.2 Animal Toxicology and/or Pharmacology

In acute studies with mice and rats, the LD50 for mice was generally > 3,600 mg/kg for oral administration and was > 2,300 mg/kg for intraperitoneal administration. In rats, the LD50 was > 2,000 mg/kg for both oral and intraperitoneal administration.

A repeated-dose toxicology study has been performed in beagle dogs using oral dosing of tinidazole at 100 mg/kg/day, 300 mg/kg/day, and 1000 mg/kg/day for 28-days. On Day 18 of the study, the highest dose was lowered to 600 mg/kg/day due to severe clinical symptoms. The two compound-related effects observed in the dogs treated with tinidazole were increased atrophy of the thymus in both sexes at the middle and high doses, and atrophy of the prostate at all doses in the males. A no-adverse-effect level (NOAEL) of 100 mg/kg/day for females was determined. There was no NOAEL identified for males because of minimal atrophy of the prostate at 100 mg/kg/day (approximately 0.9-fold the highest human dose based upon plasma AUC comparisons).

14 CLINICAL STUDIES

14.1 Trichomoniasis

Tinidazole (2 g single oral dose) use in trichomoniasis has been well documented in 34 published reports from the world literature involving over 2,800 patients treated with tinidazole. In four published, blinded, randomized, comparative studies of the 2 g tinidazole single oral dose where efficacy was assessed by culture at time points post-treatment ranging from one week to one month, reported cure rates ranged from 92% (37/40) to 100% (65/65) (n=172 total subjects). In four published, blinded, randomized, comparative studies where efficacy was assessed by wet mount between 7-14 days post-treatment, reported cure rates ranged from 80% (8/10) to 100% (16/16) (n=116 total subjects). In these studies, tinidazole was superior to placebo and comparable to other anti-trichomonal drugs. The single oral 2 g tinidazole dose was also assessed in four open-label trials in men (one comparative to metronidazole and 3 single-arm studies). Parasitological evaluation of the urine was performed both pre- and post-treatment and reported cure rates ranged from 83% (25/30) to 100% (80/80) (n=142 total subjects).

14.2 Giardiasis

Tinidazole (2 g single dose) use in giardiasis has been documented in 19 published reports from the world literature involving over 1,600 patients (adults and pediatric patients). In eight controlled studies involving a total of 619 subjects of whom 299 were given the 2 g × 1 day (50 mg/kg × 1 day in pediatric patients) oral dose of tinidazole, reported cure rates ranged from 80% (40/50) to 100% (15/15). In three of these trials where the comparator was 2 to 3 days of various doses of metronidazole, reported cure rates for metronidazole were 76% (19/25) to 93% (14/15). Data comparing a single 2 g dose of tinidazole to usually recommended 5-7 days of metronidazole are limited.

14.3 Intestinal Amebiasis

Tinidazole use in intestinal amebiasis has been documented in 26 published reports from the world literature involving over 1,400 patients. Most reports utilized tinidazole 2 g/day × 3 days. In four published, randomized, controlled studies (1 investigator single-blind, 3 open-label) of the 2 g/day × 3 days oral dose of tinidazole, reported cure rates after 3 days of therapy among a total of 220 subjects ranged from 86% (25/29) to 93% (25/27).

14.4 Amebic Liver Abscess

Tinidazole use in amebic liver abscess has been documented in 18 published reports from the world literature involving over 470 patients. Most reports utilized tinidazole 2 g/day × 2-5 days. In seven published, randomized, controlled studies (1 double-blind, 1 single-blind, 5 open-label) of the 2 g/day × 2-5 days oral dose of tinidazole accompanied by aspiration of the liver abscess when clinically necessary, reported cure rates among 133 subjects ranged from 81% (17/21) to 100% (16/16). Four of these studies utilized at least 3 days of tinidazole.

14.5 Bacterial Vaginosis

A randomized, double-blind, placebo-controlled clinical trial in 235 non-pregnant women was conducted to evaluate the efficacy of tinidazole for the treatment of bacterial vaginosis. A clinical diagnosis of bacterial vaginosis was based on Amsel's criteria and defined by the presence of an abnormal homogeneous vaginal discharge that (a) has a pH of greater than 4.5, (b) emits a "fishy" amine odor when mixed with a 10% KOH solution, and (c) contains ≥20% clue cells on microscopic examination. Clinical cure required a return to normal vaginal discharge and resolution of all Amsel's criteria. A microbiologic diagnosis of bacterial vaginosis was based on Gram stain of the vaginal smear demonstrating (a) markedly reduced or absent Lactobacillus morphology, (b) predominance of Gardnerella morphotype, and (c) absent or few white blood cells, with quantification of these bacterial morphotypes to determine the Nugent score, where a score ≥4 was required for study inclusion and a score of 0-3 considered a microbiologic cure. Therapeutic cure was a composite endpoint, consisting of both a clinical cure and microbiologic cure. In patients with all four Amsel's criteria and with a baseline Nugent score ≥4, tinidazole oral tablets given as either 2 g once daily for 2 days or 1 g once daily for 5 days demonstrated superior efficacy over placebo tablets as measured by therapeutic cure, clinical cure, and a microbiologic cure.

Table 2. Efficacy of Tindamax in the Treatment of Bacterial Vaginosis in a Randomized, Double-Blind, Double-Dummy, Placebo-Controlled Trial: Modified Intent-to-Treat Population^1 (n=227)
Outcome | Tindamax 1 g × 5 days (n=76) | Tindamax 2 g × 2 days (n=73) | Placebo (n=78)
 | % Cure | % Cure | % Cure
Therapeutic Cure Difference^2 97.5% CI^3 | 36.8 31.7 (16.8, 46.6) | 27.4 22.3 (8.0, 36.6) | 5.1
Clinical Cure Difference^2 97.5% CI^3 | 51.3 39.8 (23.3, 56.3) | 35.6 24.1 (7.8, 40.3) | 11.5
Nugent Score Cure Difference^2 97.5% CI^3 | 38.2 33.1 (18.1, 48.0) | 27.4 22.3 (8.0, 36.6) | 5.1

^1Modified Intent-to-Treat defined as all patients randomized with a baseline
Nugent score of at least 4
^2Difference in cure rates (Tindamax-placebo)
^3CI: confidence interval
p-values for both Tindamax regimens vs. placebo for therapeutic, clinical and
Nugent score cure rates for both 2 and 5 days <0.001

The therapeutic cure rates reported in this clinical study conducted with Tindamax were based on resolution of 4 out of 4 Amsel's criteria and a Nugent score of <4. The cure rates for previous clinical studies with other products approved for bacterial vaginosis were based on resolution of either 2 or 3 out of 4 Amsel's criteria. At the time of approval for other products for bacterial vaginosis, there was no requirement for a Nugent score on Gram stain, resulting in higher reported rates of cure for bacterial vaginosis for those products than for those reported here for tinidazole.

16 HOW SUPPLIED/STORAGE AND HANDLING

Tindamax 250 mg tablets are pink, round, scored tablets, with TM debossed on one side and 250 on the other, supplied in bottles with child-resistant caps as:

NDC 0178-8250-40 Bottle of 40

Tindamax 500 mg tablets are pink, oval, scored tablets, with TM debossed on one side and 500 on the other, supplied in bottles with child-resistant caps as:

NDC 0178-8500-60 Bottle of 60
NDC 0178-8500-20 Bottle of 20

Professional Samples:

NDC 0178-8500-04 Bottle of 4

STORAGE AND HANDLING

Storage: Store at controlled room temperature 20-25° C (68-77° F); excursions permitted to 15-30° C (59-86° F) [see USP]. Protect contents from light.

17 PATIENT COUNSELING INFORMATION

17.1 Administration of Drug

Patients should be told to take Tindamax with food to minimize the incidence of epigastric discomfort and other gastrointestinal side-effects. Food does not affect the oral bioavailability of tinidazole.

17.2 Alcohol Avoidance

Patients should be told to avoid alcoholic beverages and preparations containing ethanol or propylene glycol during Tindamax therapy and for 3 days afterward because abdominal cramps, nausea, vomiting, headaches, and flushing may occur.

17.3 Drug Resistance

Patients should be counseled that antibacterial drugs including Tindamax should only be used to treat bacterial infections. They do not treat viral infections (e.g., the common cold). When Tindamax is prescribed to treat a bacterial infection, patients should be told that although it is common to feel better early in the course of therapy, the medication should be taken exactly as directed. Skipping doses or not completing the full course of therapy may (1) decrease the effectiveness of the immediate treatment and (2) increase the likelihood that bacteria will develop resistance and will not be treatable by Tindamax or other antibacterial drugs in the future.

Tindamax Label
0178-8500-20

Tindamax Label
NDC: 0178-8250-40